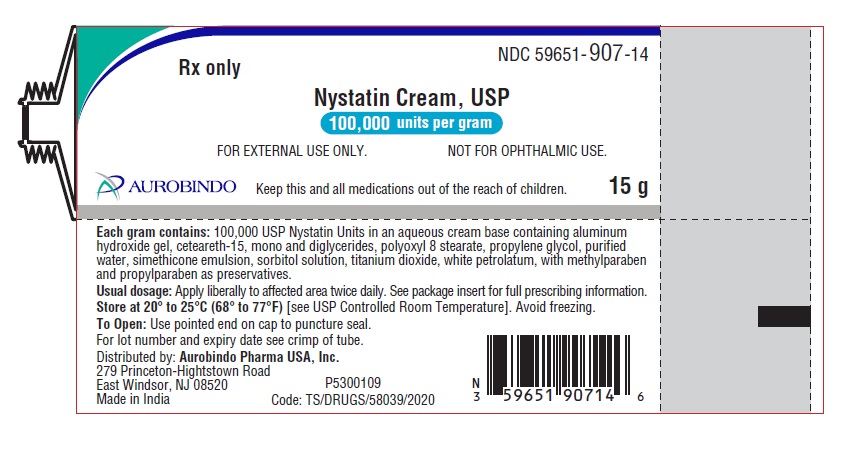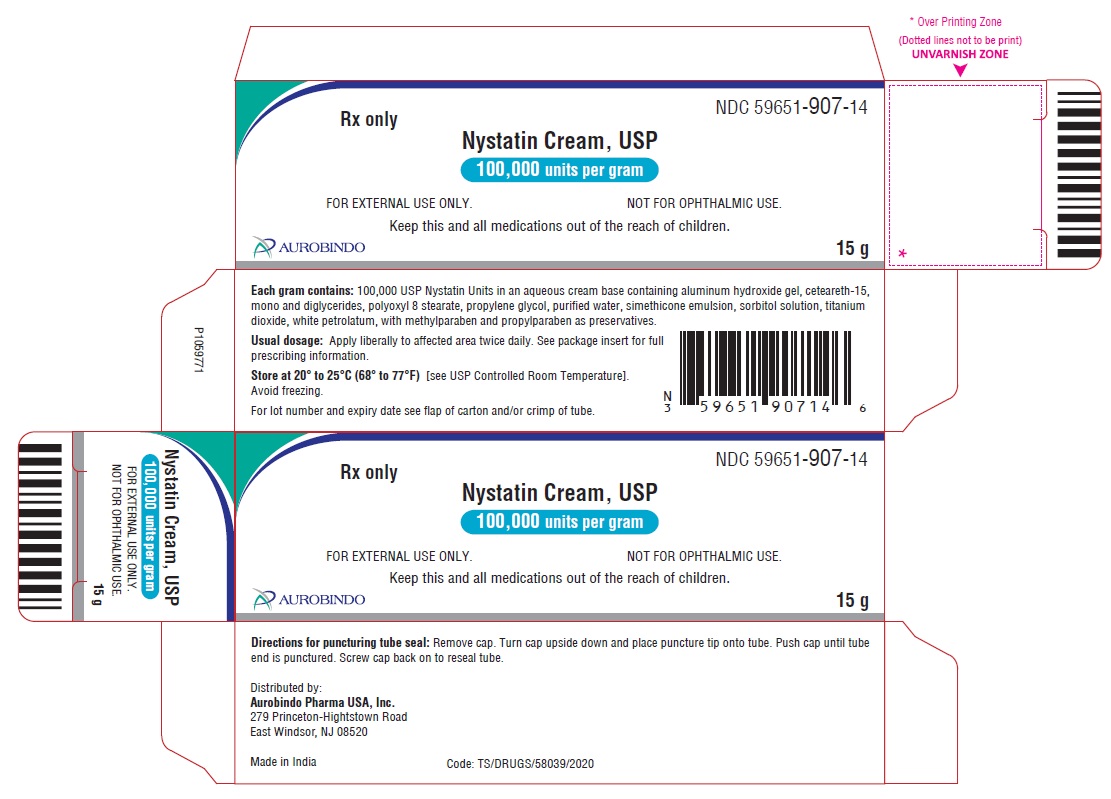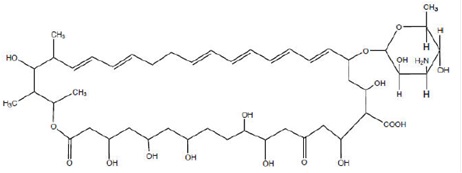 DRUG LABEL: NYSTATIN
NDC: 59651-907 | Form: CREAM
Manufacturer: Aurobindo Pharma Limited
Category: prescription | Type: Human Prescription Drug Label
Date: 20250618

ACTIVE INGREDIENTS: NYSTATIN 100000 [USP'U]/1 g
INACTIVE INGREDIENTS: ALGELDRATE; CETEARETH-15; GLYCERYL MONO- AND DIPALMITOSTEARATE; PEG-8 MONOSTEARATE; PROPYLENE GLYCOL; DIMETHICONE, UNSPECIFIED; SORBITOL SOLUTION; TITANIUM DIOXIDE; WHITE PETROLATUM; METHYLPARABEN; PROPYLPARABEN; WATER

Nystatin Cream USP, 100,000 units per gram
Rx only
FOR TOPICAL USE ONLY
NOT FOR OPHTHALMIC USE

DESCRIPTION

Nystatin is a polyene antifungal antibiotic obtained from Streptomyces nursei.

Structural formula:

C47H75NO17 Molecular Weight: 926.13

Nystatin cream is for dermatologic use.

Nystatin cream for topical use, contains 100,000 USP nystatin units per gram in an aqueous, cream base containing aluminum hydroxide gel, ceteareth-15, mono and diglycerides, polyoxyl 8 stearate, propylene glycol, purified water, simethicone emulsion, sorbitol solution, titanium dioxide, white petrolatum, with methylparaben and propylparaben as preservatives.

CLINICAL PHARMACOLOGY

Pharmacokinetics

Nystatin is not absorbed from intact skin or mucous membrane.

Microbiology

Nystatin is an antibiotic which is both fungistatic and fungicidal in vitro against a wide variety of yeasts and yeast-like fungi, including Candida albicans, C. parapsilosis, C. tropicalis, C. guilliermondi, C. pseudotropicalis, C. krusei, Torulopsis glabrata, Tricophyton rubrum, T. mentagrophytes.

Nystatin acts by binding to sterols in the cell membrane of susceptible species resulting in a change in membrane permeability and the subsequent leakage of intracellular components. On repeated subculturing with increasing levels of nystatin, Candida albicans does not develop resistance to nystatin. Generally, resistance to nystatin does not develop during therapy. However, other species of Candida (C. tropicalis, C. guilliermondi, C. krusei, and C. stellatoides) become quite resistant on treatment with nystatin and simultaneously become cross resistant to amphotericin as well. This resistance is lost when the antibiotic is removed. Nystatin exhibits no appreciable activity against bacteria, protozoa, or viruses.

INDICATIONS AND USAGE

Nystatin cream is indicated in the treatment of cutaneous or mucocutaneous mycotic infections caused by Candida albicans and other susceptible Candida species.

This cream is not indicated for systemic, oral, intravaginal or ophthalmic use.

CONTRAINDICATIONS

Nystatin cream is contraindicated in patients with a history of hypersensitivity to any of its components.

PRECAUTIONS

General

Nystatin cream should not be used for the treatment of systemic, oral, intravaginal or ophthalmic infections.

If irritation or sensitization develops, treatment should be discontinued and appropriate measures taken as indicated. It is recommended that KOH smears, cultures, or other diagnostic methods be used to confirm the diagnosis of cutaneous or mucocutaneous candidiasis and to rule out infection caused by other pathogens.

INFORMATION FOR THE PATIENT

Patients using this medication should receive the following information and instructions:

1. The patient should be instructed to use this medication as directed (including the replacement of missed doses). This medication is not for any disorder other than that for which it is prescribed.
2. Even if symptomatic relief occurs within the first few days of treatment, the patient should be advised not to interrupt or discontinue therapy until the prescribed course of treatment is completed.
3. If symptoms of irritation develop, the patient should be advised to notify the physician promptly.

Laboratory Tests

If there is a lack of therapeutic response, KOH smears, cultures, or other diagnostic methods should be repeated.

Carcinogenesis, Mutagenesis, Impairment of Fertility

No long-term animal studies have been performed to evaluate the carcinogenic potential of nystatin. No studies have been performed to determine the mutagenicity of nystatin or the effects on male or female fertility.

Pregnancy

Animal reproduction studies have not been conducted with any nystatin cream. It also is not known whether this cream can cause fetal harm when used by a pregnant woman or can affect reproductive capacity. Nystatin cream should be prescribed for a pregnant woman only if the potential benefit to the mother outweighs the potential risk to the fetus.

Nursing Mothers

It is not known whether nystatin is excreted in human milk. Caution should be exercised when nystatin is prescribed for a nursing woman.

Pediatric Use

Safety and effectiveness have been established in the pediatric population from birth to 16 years. (See DOSAGE AND ADMINISTRATION.)

Geriatric Use

Clinical studies with nystatin cream did not include sufficient numbers of subjects aged 65 years and older to determine whether they respond differently than younger subjects. Other reported clinical experience has not identified differences in responses between elderly and younger patients, but greater sensitivity of some older individuals cannot be ruled out.

ADVERSE REACTIONS

The frequency of adverse events reported in patients using nystatin cream is less than 0.1%. The more common events that were reported include allergic reactions, burning, itching, rash, eczema, and pain on application. (See PRECAUTIONS: General.)

DOSAGE AND ADMINISTRATION

Adults and Pediatric Patients (Neonates and Older)

Apply liberally to affected areas twice daily or as indicated until healing is complete.

HOW SUPPLIED

Nystatin Cream USP is yellow to light green smooth cream and supplied as follows:

Tube of 15 g NDC 59651-907-14

Tube of 30 g NDC 59651-907-30

Store at 20° to 25°C (68° to 77°F) [see USP Controlled Room Temperature]. Avoid freezing.

Distributed by:
Aurobindo Pharma USA, Inc.
279 Princeton-Hightstown Road
East Windsor, NJ 08520

Manufactured by:
Aurobindo Pharma Limited
Hyderabad-500 032, India

Issued: May 2024

PACKAGE LABEL-PRINCIPAL DISPLAY PANEL - 15 g Tube Label

NDC 59651-907-14
Rx only
Nystatin Cream, USP
100,000 units per gram
FOR EXTERNAL USE ONLY. NOT FOR OPHTHALMIC USE.
AUROBINDO Keep this and all medications out of the reach of children. 15 g

PACKAGE LABEL-PRINCIPAL DISPLAY PANEL - 15 g Tube Carton Label

NDC 59651-907-14
Rx only
Nystatin Cream, USP
100,000 units per gram
FOR EXTERNAL USE ONLY. NOT FOR OPHTHALMIC USE.

Keep this and all medications out of the reach of children.

AUROBINDO 15 g